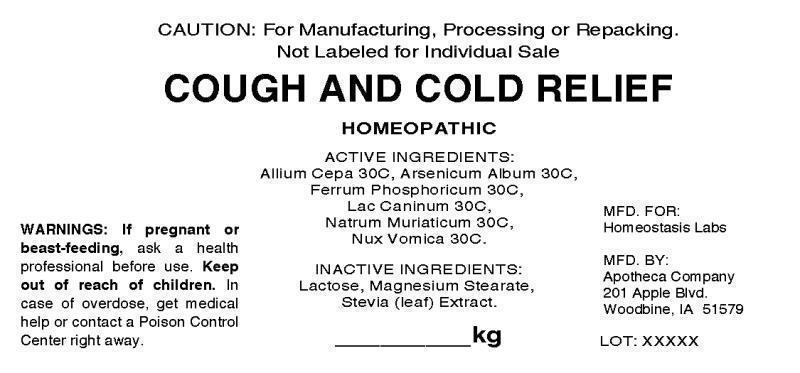 DRUG LABEL: Cough and Cold Relief
NDC: 57520-1251 | Form: TABLET
Manufacturer: Apotheca Company
Category: homeopathic | Type: HUMAN OTC DRUG LABEL
Date: 20130830

ACTIVE INGREDIENTS: ONION 30 [hp_C]/1 1; ARSENIC TRIOXIDE 30 [hp_C]/1 1; FERROSOFERRIC PHOSPHATE 30 [hp_C]/1 1; CANIS LUPUS FAMILIARIS MILK 30 [hp_C]/1 1; SODIUM CHLORIDE 30 [hp_C]/1 1; STRYCHNOS NUX-VOMICA SEED 30 [hp_C]/1 1
INACTIVE INGREDIENTS: LACTOSE; MAGNESIUM STEARATE; STEVIA LEAF

DRUG FACTS:

ACTIVE INGREDIENTS:

Allium Cepa 30C, Arsenicum Album 30C, Ferrum Phosphoricum 30C, Lac Caninum 30C, Natrum Muricaticum 30C, Nux Vomica 30C

INDICATIONS:

CAUTION: For Manufacturing, Processing or Repacking.

Not Labeled for Individual Sale

WARNINGS:

If pregnant or breast-feeding, ask a health professional before use.

Keep out of reach of children. In case of overdose, get medical help or contact a Poison Control Center right away.

Keep out of reach of children. In case of overdose, get medical help or contact a Poison Control Center right away.

DIRECTIONS:

TO BE DETERMINED BY FINAL PROCESSOR.

INDICATIONS:

CAUTION: For Manufacturing, Processing or Repacking.

Not Labeled for Individual Sale

INACTIVE INGREDIENTS:

Lactose, Magnesium Stearate, Stevia (leaf) Extract

QUESTIONS:

MFD. FOR:

Homeostasis Labs

MFD. BY:

Apotheca Company

201 Apple Blvd.

Woodbine, IA 51579

PACKAGE DISPLAY LABEL:

CAUTION: For Manufacturing, Processing or Repacking.

Not Labeled for Individual Sale

COUGH AND COLD RELIEF

HOMEOPATHIC